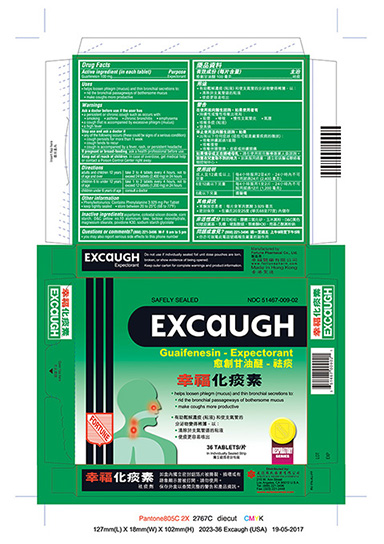 DRUG LABEL: EXCAUGH
NDC: 51467-009 | Form: TABLET
Manufacturer: FORTUNE PHARMACAL COMPANY, LIMITED
Category: otc | Type: HUMAN OTC DRUG LABEL
Date: 20251113

ACTIVE INGREDIENTS: GUAIFENESIN 100 mg/1 1
INACTIVE INGREDIENTS: ASPARTAME; SILICON DIOXIDE; STARCH, CORN; D&C YELLOW NO. 10; LACTOSE MONOHYDRATE; MAGNESIUM STEARATE; POVIDONE K30; SODIUM STARCH GLYCOLATE TYPE A POTATO

Drug Facts

Active ingredients (in each tablet)
Guaifenesin 100 mg

Purpose
Expectorant

Uses
helps loosen phlegm (mucus) and thin bronchial secretions to:
rid the bronchial passageways of bothersome mucus
make coughs more productive

Warnings

Ask a doctor before use if the user has
a persistent or chronic cough such as occurs with:
smoking
asthma
chronic bronchitis
emphysema
a cough that is accompanied by excessive phlegm (mucus)
a high fever

Stop use and ask a doctor if
any of the following occurs (these could be signs of a serious condition):
cough persists for more than 1 week
cough tends to recur
cough is accompanied by a fever, rash, or persistent headache

PREGNANCY OR BREAST FEEDING

If pregnant or breast-feeding, ask a health professional before use.

Keep out of reach of children.In case of overdose, get medical help or contact a Poison Control Center right away.

Directions
adults and children 12 years of age and over: take 2 to 4 tablets every 4 hours, not to exceed 24 tablets (2,400 mg) in 24 hours
children 6 to under 12 years of age: take 1 to 2 tablets every 4 hours, not to exceed 12 tablets (1,200 mg) in 24 hours
children under 6 years of age: consult a doctor

Other information
Phenylketonurics: Contains Phenylalanine 3.929 mg Per Tablet
keep tightly sealed
store between 20 to 25º C (68 to 77º F)

INACTIVE INGREDIENT

Inactive ingredientsaspartame, colloidal silicon dioxide, corn starch, D&C yellow no.10 aluminum lake, lactose monohydrate, magnesium stearate, povidone K30, sodium starch glycolate.

Questions or comments?(888) 221-3496 M-F 9 am to 5 pm
you may also report serious side effects to this phone number

PACKAGE LABEL

EXCAUGH
Guaifenesin - Expectorant
NDC 51467-009-02
36 Tablets